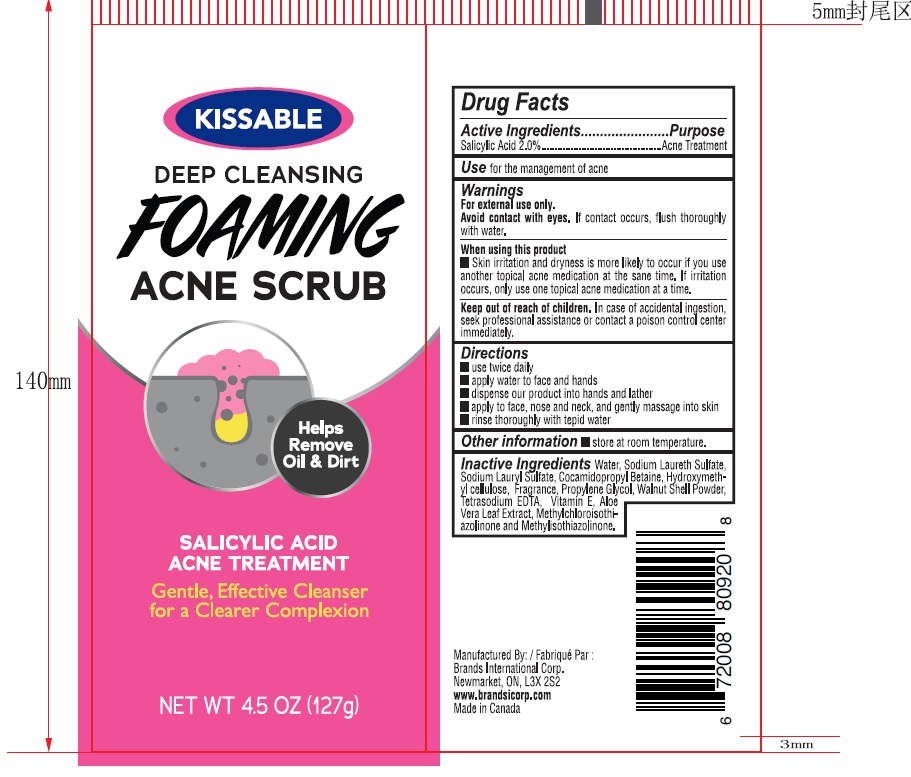 DRUG LABEL: Deep cleansing foaming acne scrub
NDC: 50157-609 | Form: LIQUID
Manufacturer: Brands International Corporation
Category: otc | Type: HUMAN OTC DRUG LABEL
Date: 20230222

ACTIVE INGREDIENTS: SALICYLIC ACID 2 g/1 mL
INACTIVE INGREDIENTS: WATER; SODIUM LAURETH SULFATE; COCAMIDOPROPYL BETAINE; SODIUM LAURYL SULFATE; HYDROXYMETHYL CELLULOSE; DITETRACYCLINE TETRASODIUM EDETATE; METHYLCHLOROISOTHIAZOLINONE; METHYLISOTHIAZOLINONE; BLACK WALNUT SHELL; VITAMIN E POLYETHYLENE GLYCOL SUCCINATE; ALOE VERA LEAF

KISSABLE - Deep cleansing Foaming Acne Scrub

ACTIVE INGREDIENT

Salicylic Acid 2.0%.

PURPOSE

Acne Treatment

DOSAGE AND ADMINISTRATION

Direction

- use twice daily
- apply water to face and hands
- dispense our product into hands and lather
- apply to face, nose, and neck, and gently massage into skin
- rinse thoroughly with tepid water

Indications and Use

For management of Acne

WARNINGS

For external use only

Avoid contact with eyes. If contact occurs, flush thoroughly with water

Stop use and ask a doctor if irritation or redness develops

When using this product

- skin irritation and dryness is more likely to occur if you use another topical acne medication at the same time
- if irritation occurs, only use one topical acne medication at a time.

Keep out of reach of children

In case of accidental ingestion, seek professional assistance or contact a poison control center immediately.

INACTIVE INGREDIENT

Water, Sodium Laureth Sulfate, Cocamidopropyl Betaine, Sodium Lauryl Sulfate, Hydroxymethyl cellulose, Fragrance, Tetrasodium EDTA, Methylchloroisothiazolinone, Methylisothiazolinone, Walnut Shell Powder, Vitamin E, Aloe Vera Leaf Extract.

OTHER SAFETY INFORMATION

Store at room temperature.